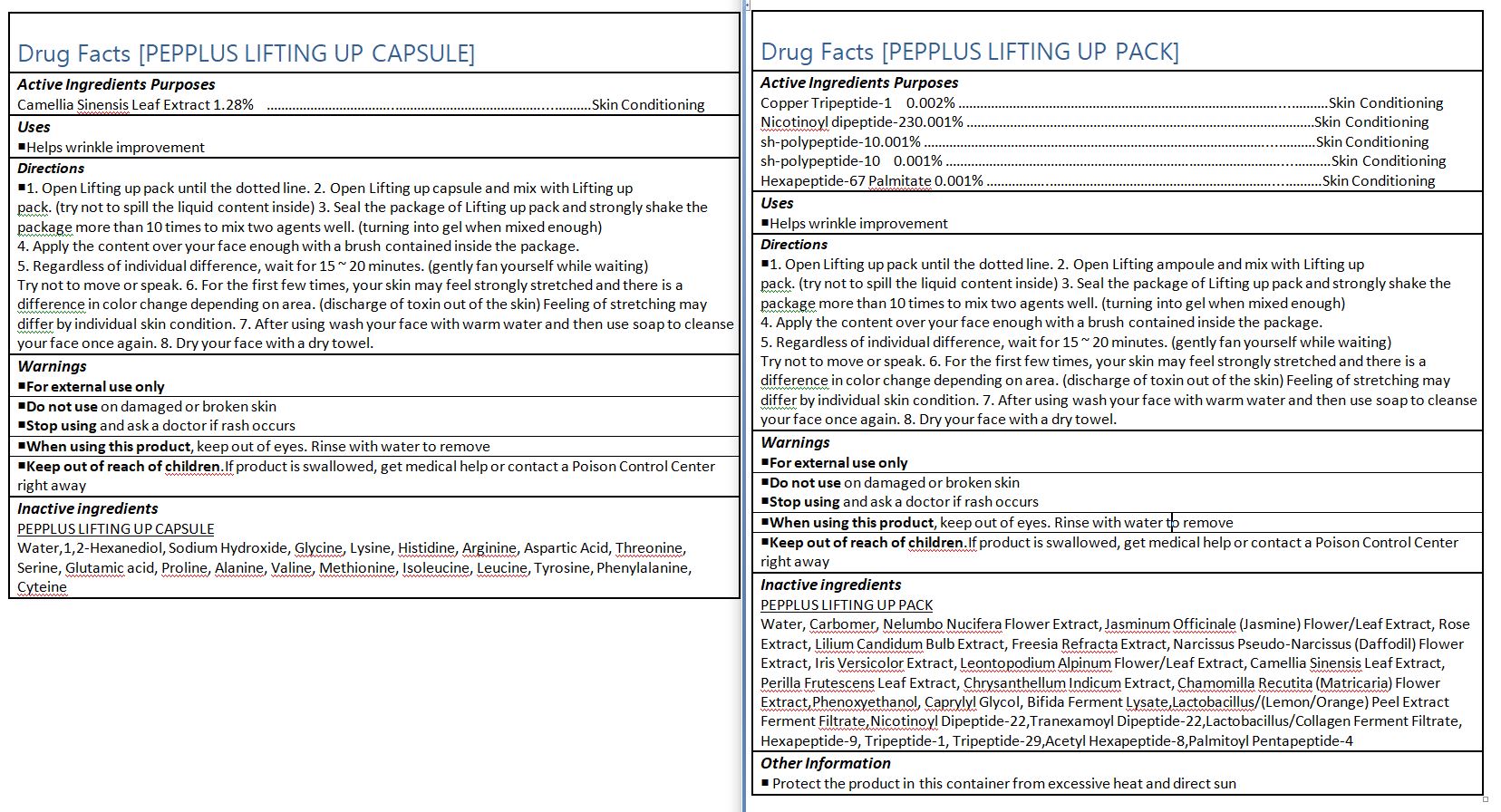 DRUG LABEL: PEPPLUS SPECIAL SKIN CARE LIFTING PROGRAM
NDC: 72211-008 | Form: KIT | Route: TOPICAL
Manufacturer: Picobio Co., Ltd.
Category: otc | Type: HUMAN OTC DRUG LABEL
Date: 20211102

ACTIVE INGREDIENTS: BASIC FIBROBLAST GROWTH FACTOR (HUMAN) 0.001 g/100 mL; PREZATIDE COPPER 0.002 g/100 mL; GREEN TEA LEAF 1.28 g/100 mL
INACTIVE INGREDIENTS: WATER; NELUMBO NUCIFERA FLOWER OIL; WATER; 1,2-HEXANEDIOL

72211-006,007,008

ACTIVE INGREDIENT

Copper Tripeptide-1, Nicotinoyl dipeptide-230, sh-polypeptide-10, Hexapeptide-67 Palmitate, Camellia Sinensis Leaf Extract

INACTIVE INGREDIENT

PEPPLUS LIFTING UP CAPSULE

Water,1,2-Hexanediol, Sodium Hydroxide, Glycine, Lysine, Histidine, Arginine, Aspartic Acid, Threonine, Serine, Glutamic acid, Proline, Alanine, Valine, Methionine, Isoleucine, Leucine, Tyrosine, Phenylalanine, Cyteine

PEPPLUS LIFTING UP PACK

Water, Carbomer, Nelumbo Nucifera Flower Extract, Jasminum Officinale (Jasmine) Flower/Leaf Extract, Rose Extract, Lilium Candidum Bulb Extract, Freesia Refracta Extract, Narcissus Pseudo-Narcissus (Daffodil) Flower Extract, Iris Versicolor Extract, Leontopodium Alpinum Flower/Leaf Extract, Camellia Sinensis Leaf Extract, Perilla Frutescens Leaf Extract, Chrysanthellum Indicum Extract, Chamomilla Recutita (Matricaria) Flower Extract,Phenoxyethanol, Caprylyl Glycol, Bifida Ferment Lysate,Lactobacillus/(Lemon/Orange) Peel Extract Ferment Filtrate,Nicotinoyl Dipeptide-22,Tranexamoyl Dipeptide-22,Lactobacillus/Collagen Ferment Filtrate, Hexapeptide-9, Tripeptide-1, Tripeptide-29,Acetyl Hexapeptide-8,Palmitoyl Pentapeptide-4

PURPOSE

Helps wrinkle improvement

Keep out of reach of the children

INDICATIONS AND USAGE

1. Open Lifting up pack until the dotted line. 2. Open Lifting up capsule and mix with Lifting up

pack. (try not to spill the liquid content inside) 3. Seal the package of Lifting up pack and strongly shake the

package more than 10 times to mix two agents well. (turning into gel when mixed enough)

4. Apply the content over your face enough with a brush contained inside the package.

5. Regardless of individual difference, wait for 15 ~ 20 minutes. (gently fan yourself while waiting)

Try not to move or speak. 6. For the first few times, your skin may feel strongly stretched and there is a

difference in color change depending on area. (discharge of toxin out of the skin) Feeling of stretching may

differ by individual skin condition. 7. After using wash your face with warm water and then use soap to cleanse your face once again. 8. Dry your face with a dry towel.

WARNINGS

1. Do not use in the following cases(Eczema and scalp wounds)
2.Side Effects
1)Due to the use of this druf if rash, irritation, itching and symptopms of hypersnesitivity occur dicontinue use and consult your phamacisr or doctor
3.General Precautions
1)If in contact with the eyes, wash out thoroughty with water If the symptoms are servere, seek medical advice immediately
2)This product is for exeternal use only. Do not use for internal use
4.Storage and handling precautions
1)If possible, avoid direct sunlight and store in cool and area of low humidity
2)In order to maintain the quality of the product and avoid misuse
3)Avoid placing the product near fire and store out in reach of children

DOSAGE AND ADMINISTRATION

for external use only